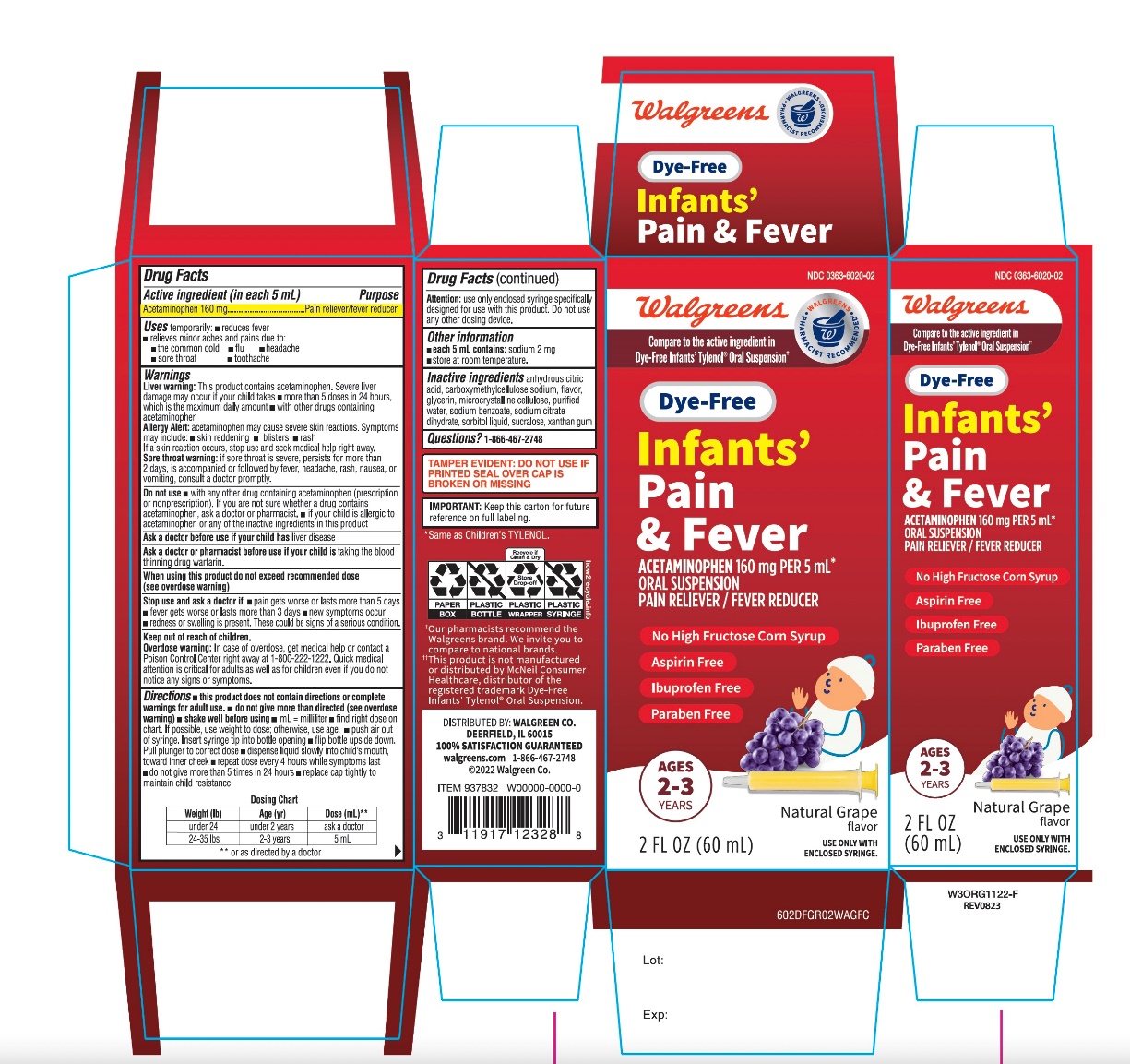 DRUG LABEL: Dye FreeInfants Pain and Fever
NDC: 0363-6020 | Form: SUSPENSION
Manufacturer: WALGREEN COMPANY
Category: otc | Type: HUMAN OTC DRUG LABEL
Date: 20251201

ACTIVE INGREDIENTS: ACETAMINOPHEN 160 mg/5 mL
INACTIVE INGREDIENTS: ANHYDROUS CITRIC ACID; CARBOXYMETHYLCELLULOSE SODIUM, UNSPECIFIED; GLYCERIN; MICROCRYSTALLINE CELLULOSE; WATER; SODIUM BENZOATE; SODIUM CITRATE, UNSPECIFIED FORM; SORBITOL SOLUTION; SUCRALOSE; XANTHAN GUM

Walgreen Dye-Free Infants' Pain + Fever Drug Facts

Drug Facts

Active ingredient (in each 5 mL)

Acetaminophen 160 mg

Purpose

Pain reliever/fever reducer

Uses

temporarily:

- reduces fever
- relieves minor aches and pains due to:
  - the common cold
  - flu
  - headache
  - sore throat
  - toothache

Warnings

Liver warning

This product contains acetaminophen. Severe liver damage may occur if your child takes

- more than 5 doses in 24 hours, which is the maximum daily amount
- with other drugs containing acetaminophen

Allergy alert:acetaminophen may cause severe skin reactions.

Symptoms may include:

- skin reddening
- blisters
- rash

If a skin reaction occurs, stop use and seek medical help right away.

Sore throat warning:if sore throat is severe, persists for more than 2 days, is accompanied or followed by fever, headache, rash, nausea, or vomiting, consult a doctor promptly.

Do not use

- with any other drug containing acetaminophen (prescription or nonprescription). If you are not sure whether a drug contains acetaminophen, ask a doctor or pharmacist.
- if your child is allergic to acetaminophen or any of the inactive ingredients in this product

Ask a doctor before use if your child hasliver disease

Ask a doctor or pharmacist before use if your child istaking the blood thinning drug warfarin

When using this product do not exceed recommended dose (see overdose warning)

Stop use and ask a doctor if

- pain gets worse or lasts more than 5 days
- fever gets worse or lasts more than 3 days
- new symptoms occur
- redness or swelling is present

These could be signs of a serious condition.

Keep out of reach of children.

Overdose warning

In case of overdose, get medical help or contact a Poison Control Center right away. (1-800-222-1222) Quick medical attention is critical for adults as well as for children even if you do not notice any signs or symptoms.

Directions

- this product does not contain directions or complete warnings for adult use.
- do not give more than directed (see overdose warning)
- shake well before using
- mL = milliliter
- find right dose on chart. If possible, use weight to dose; otherwise, use age.
- push air out of syringe. Insert syringe tip into bottle opening
- flip bottle upside down. Pull yellow part of syringe to correct dose
- dispense liquid slowly into child's mouth, toward inner cheek
- repeat dose every 4 hours while symptoms last
- do not give more than 5 times in 24 hours
- replace cap tightly to maintain child resistance

Dosing Chart
Weight (lb) | Age (yr) | Dose (mL) **
under 24 | under 2 years | ask a doctor
24-35 lbs | 2-3 years | 1. mL

Attention:use only enclosed syringe specifically designed for use with this product.

Do not use any other dosing device.

Other information

- store at room temperature
- Each 5 mL contains:sodium 2 mg

Inactive ingredients

anhydrous citric acid, carboxymethylcellulose sodium, flavors, glycerin, microcrystalline cellulose, sodium benzoate, purified water, sodium citrate dihydrate, sorbitol liquid, sucralose, xanthan gum

Questions?

1-866-467-2748

PRINCIPAL DISPLAY PANEL

Compare to the active ingredient in Dye-Free Infants’ Tylenol® Oral Suspension*

NDC 0363-6020-02

Dye-Free

Infants'
Pain + Fever

Acetaminophen

Oral Suspension
Pain Reliever-Fever Reducer

Free Of:

- Dyes
- Sugar Free
- Ibuprofen
- Aspirin
- Parabens
- High Fructose Corn Syrup

Natural Grape Flavor

No Added Alcohol
Use Only Enclosed Syringe

2FL OZ (60mL)
160 mg per 5 mL***

***Same as Children’s TYLENOL

*This Product is not manufactured or distributed by McNeil Consumer Healthcare, distributor of the registered trademark Dye-Free Infants’ Tylenol® Oral Suspension.